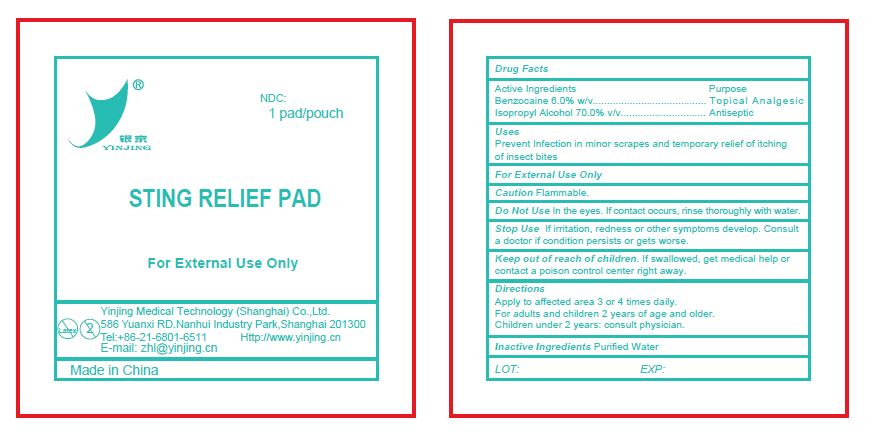 DRUG LABEL: STING RELIEF PAD
NDC: 44019-911 | Form: PATCH
Manufacturer: Yinjing Medical Technology (Shanghai) Co., Ltd.
Category: otc | Type: HUMAN OTC DRUG LABEL
Date: 20170713

ACTIVE INGREDIENTS: BENZOCAINE 0.06 g/1 mL; ISOPROPYL ALCOHOL 0.7 mL/1 mL
INACTIVE INGREDIENTS: WATER

Sting Relief Pad

Active Ingredient

Benzocaine 6.0% w/v

Isopropyl Alcohol 70.0% v/v

Purpose

Topical Analgesic

Antiseptic

Uses

Prevent infection in minor scrapes and temporary relief of itching of insect bites

Warnings

-For external use only

-Caution Flammable

-Do Not Use in the eyes. If contact occurs, rinse throughly with water.

-Stop Use if irritation, redness or other symptoms develop. Consult a doctor if condition persist or gets worse.

Keep out of reach of children.

If swallowed, get medical help or contact a poison control center right away.

Directions

Apply to affected area 3 or 4 times daily.

For Adults and children 2 years of age and older.

Children under 2 years: consult physician.

Inactive Ingridients

Purified Water